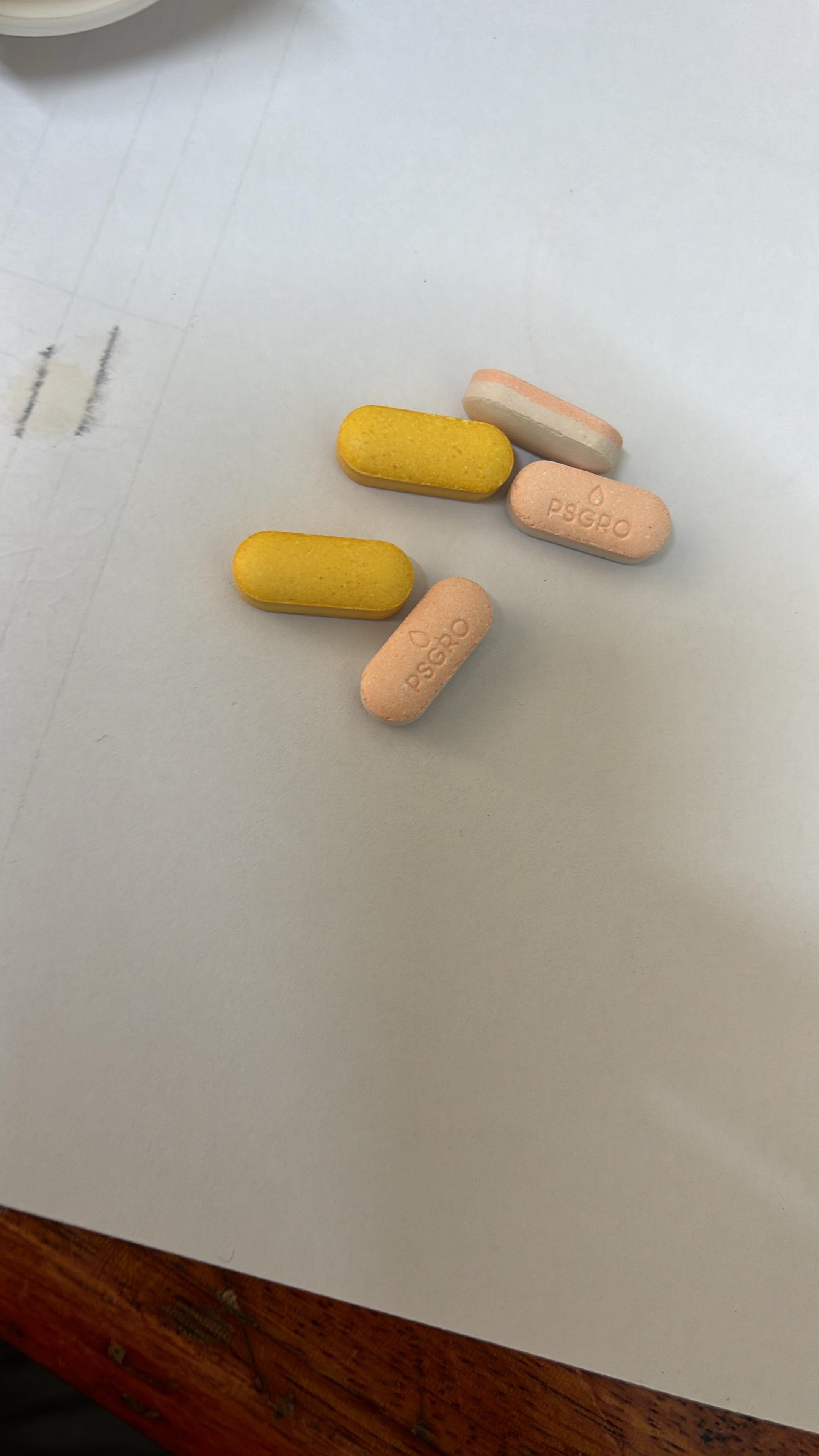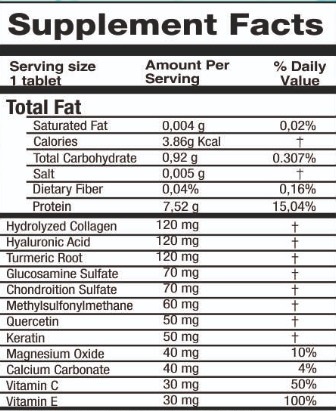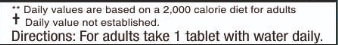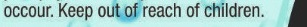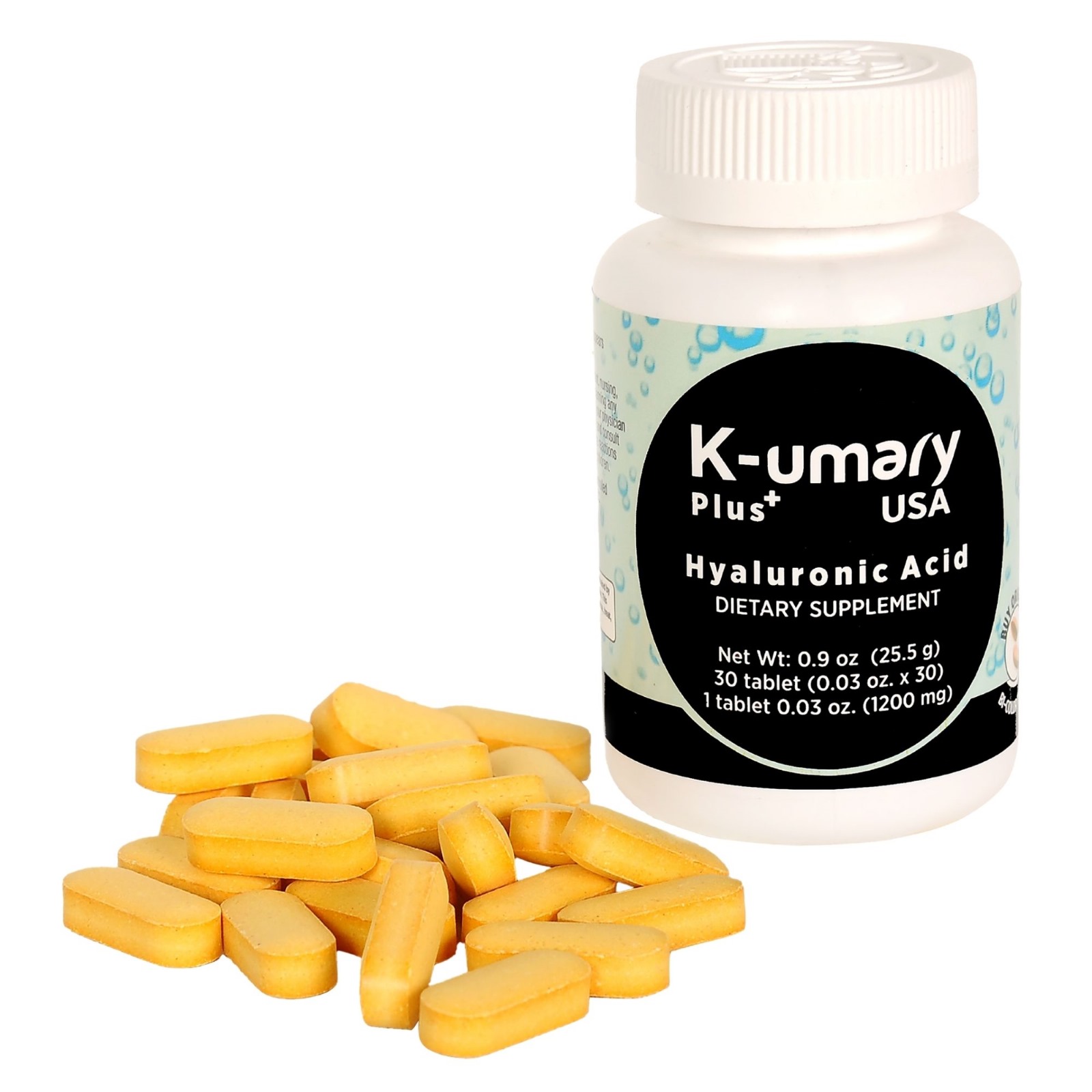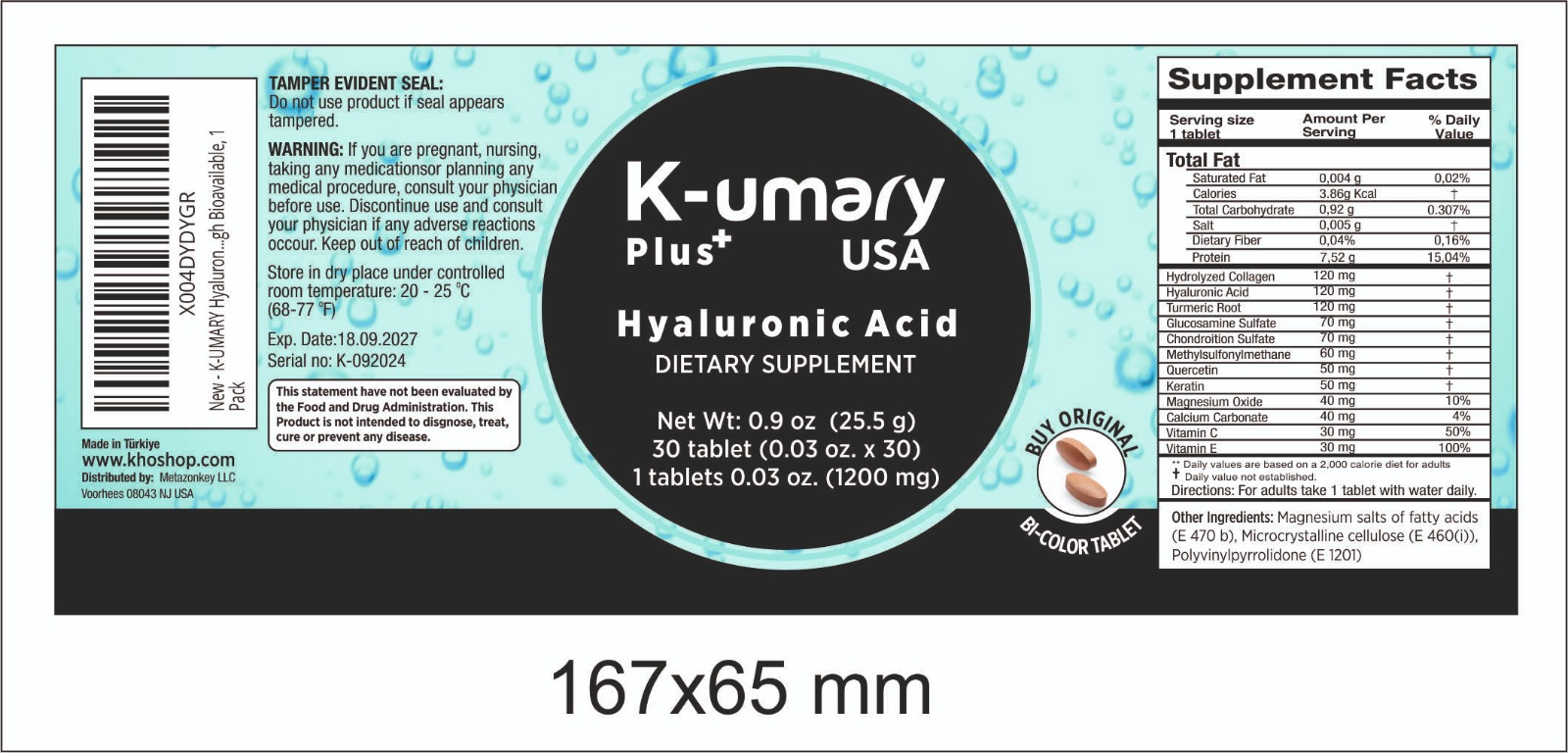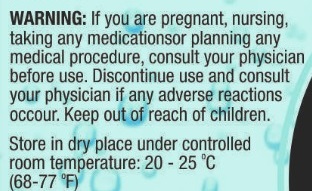 DRUG LABEL: kumary
NDC: 84858-1010 | Form: TABLET
Manufacturer: METAZONKEY LLC
Category: otc | Type: HUMAN OTC DRUG LABEL
Date: 20241105

ACTIVE INGREDIENTS: CHONDROITIN SULFATE (BOVINE) 70 mg/1 U; HYDROLYZED SHEEP WOOL KERATIN (200 MW) 50 mg/1 U; HYALURONIC ACID 120 mg/1 U; CALCIUM CARBONATE 40 mg/1 U; TURMERIC 120 mg/1 U; COLLAGEN ALPHA-2(I) CHAIN BOVINE 120 mg/1 U; MAGNESIUM OXIDE 40 mg/1 U; POVIDONE-IODINE 100 mg/1 U; MAGNESIUM STEARATE 10 mg/1 U; ASCORBIC ACID 30 mg/1 U
INACTIVE INGREDIENTS: GLUCOSAMINE SULFATE 70 mg/1 U; .ALPHA.-TOCOPHEROL ACETATE, D- 30 mg/1 U; CELLULOSE, MICROCRYSTALLINE 340 mg/1 U

DOSAGE AND ADMINISTRATION

For adults take 1 tablet with water daily

WARNINGS

WARNING: If you are pregnant, nursing, taking any medicationsor planning any medical procedure, consult your physician before use. Discontinue use and consult your physician if any adverse reactions occour. Keep out of reach of children.
Store in dry place under controlled room temperature: 20 - 25 °C
(68-77°F)